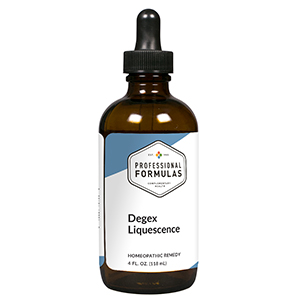 DRUG LABEL: Degex Liquescence
NDC: 63083-3025 | Form: LIQUID
Manufacturer: Professional Complementary Health Formulas
Category: homeopathic | Type: HUMAN OTC DRUG LABEL
Date: 20190815

ACTIVE INGREDIENTS: PERVINCA MINOR WHOLE 2 [hp_X]/118 mL; AVISCUMINE 3 [hp_X]/118 mL; PHYTOLACCA AMERICANA ROOT 4 [hp_X]/118 mL; GOLDENSEAL 6 [hp_X]/118 mL; CONIUM MACULATUM FLOWERING TOP 6 [hp_X]/118 mL; THUJA OCCIDENTALIS LEAF 6 [hp_X]/118 mL; UBIDECARENONE 10 [hp_X]/118 mL; GERMANIUM 10 [hp_X]/118 mL; GLYOXAL 10 [hp_X]/118 mL; LACHESIS MUTA VENOM 12 [hp_X]/118 mL; NAJA NAJA VENOM 12 [hp_X]/118 mL; PHOSPHORUS 30 [hp_X]/118 mL
INACTIVE INGREDIENTS: ALCOHOL; WATER

T25

ACTIVE INGREDIENTS

Vinca minor 2X
Viscum album 3X
Phytolacca decandra 4X
Hydrastis canadensis 6X
Conium maculatum 6X, 9X
Thuja occidentalis 6X, 9X
Coenzyme Q10 10X
Germanium 10X
Glyoxal 10X
Lachesis mutus 12X
Naja tripudians 12X
Phosphorus 30X, 60X

QUESTIONS

Professional Formulas

PO Box 2034 Lake Oswego, OR 97035

INDICATIONS

For the temporary relief of exhaustion or weakness, minor aches, pains, stiffness, or inflammation of joints or muscles, or dry, itchy skin.*

PURPOSE

*Claims based on traditional homeopathic practice, not accepted medical evidence. Not FDA evaluated.

WARNINGS

In case of overdose, get medical help or contact a poison control center right away.

Keep out of the reach of children.

PREGNANCY OR BREAST FEEDING

If pregnant or breastfeeding, ask a healthcare professional before use.

DIRECTIONS

Place drops under tongue 30 minutes before/after meals. Adults and children 12 years and over: Take one full dropper up to 2 times per day. Consult a physician for use in children under 12 years of age.

OTHER INFORMATION

Tamper resistant. If seal is broken, do not use. After opening, close container tightly and store at room temperature away from heat.

INACTIVE INGREDIENTS

20% ethanol, purified water.

LABEL

Est 1985

Professional Formulas

Complementary Health

Degex Liquescence

Homeopathic Remedy

4 FL. OZ. (118 mL)